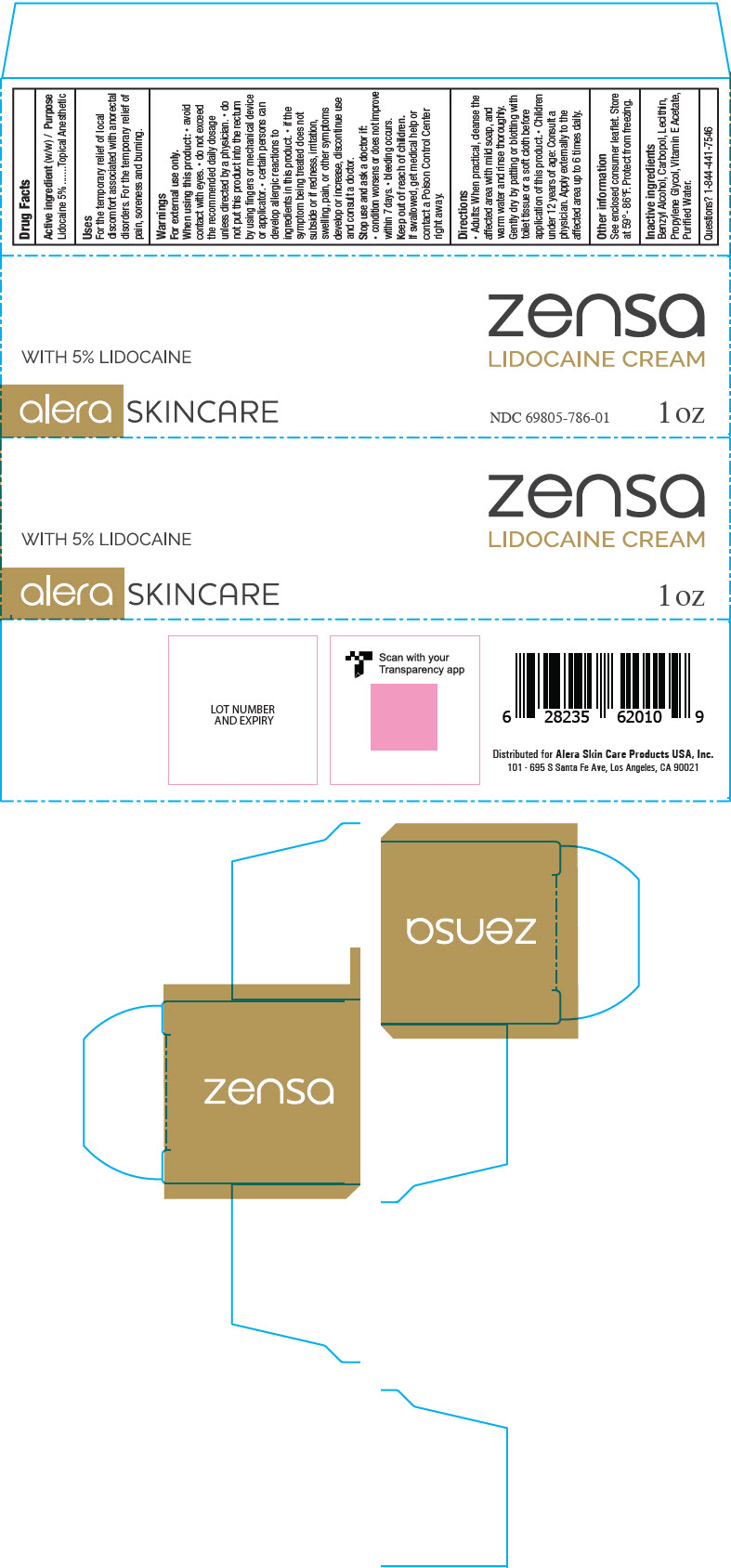 DRUG LABEL: Zensa
NDC: 69805-786 | Form: CREAM
Manufacturer: Alera Skin Care Products Inc.
Category: otc | Type: HUMAN OTC DRUG LABEL
Date: 20241124

ACTIVE INGREDIENTS: LIDOCAINE 5 g/100 g
INACTIVE INGREDIENTS: BENZYL ALCOHOL; CARBOMER HOMOPOLYMER TYPE B (ALLYL PENTAERYTHRITOL CROSSLINKED); LECITHIN, SOYBEAN; PROPYLENE GLYCOL; .ALPHA.-TOCOPHEROL ACETATE; WATER

Zensa - 5% Lidocaine Cream

Active ingredient

Lidocaine 5%

Purpose

Topical Anaesthetic

Uses

- For the temporary relief of local discomfort associated with anorectal disorders
- For the temporary relief of pain, soreness, and burning

Warnings

For external use only.

When using this product

- avoid contact with eyes
- do not exceed the recommended daily dosage unless directed by a physician
- do not put this product into the rectum by using fingers or any mechanical device or applicator
- certain persons can develop allergic reactions to ingredients in this product. If the symptom being treated does not subside or if redness, irritation, swelling, pain, or other symptoms develop or increase, discontinue use and consult a doctor

Stop use and ask a doctor if

- condition worsens or does not improve within 7 days
- bleeding occurs

Keep out of reach of children

If swallowed, get medical help or contact a Poison Control Center right away

Directions

- Adults: when practical, cleanse the affected area with mild soap, and warm water and rinse thoroughly. Gently dry by patting or blottig with toilet tissue or a soft cloth before application of this product. Children under 12 years of age: consult a physician.
- Apply externally to the affected area up to 6 times daily

Other information

See enclosed consumer leaflet.

Store at 15°C to 30°C. Protect from freezing

Inactive ingredients

Benzyl Alcohol, Carbopol, Lecithin, Propylene Glycol, Vitamin E Acetate, Purified Water

PRINCIPAL DISPLAY PANEL - 1 oz Tube Carton

zensa
LIDOCAINE CREAM

WITH 5% LIDOCAINE

alera SKINCARE

NDC 69805-786-01
1 oz